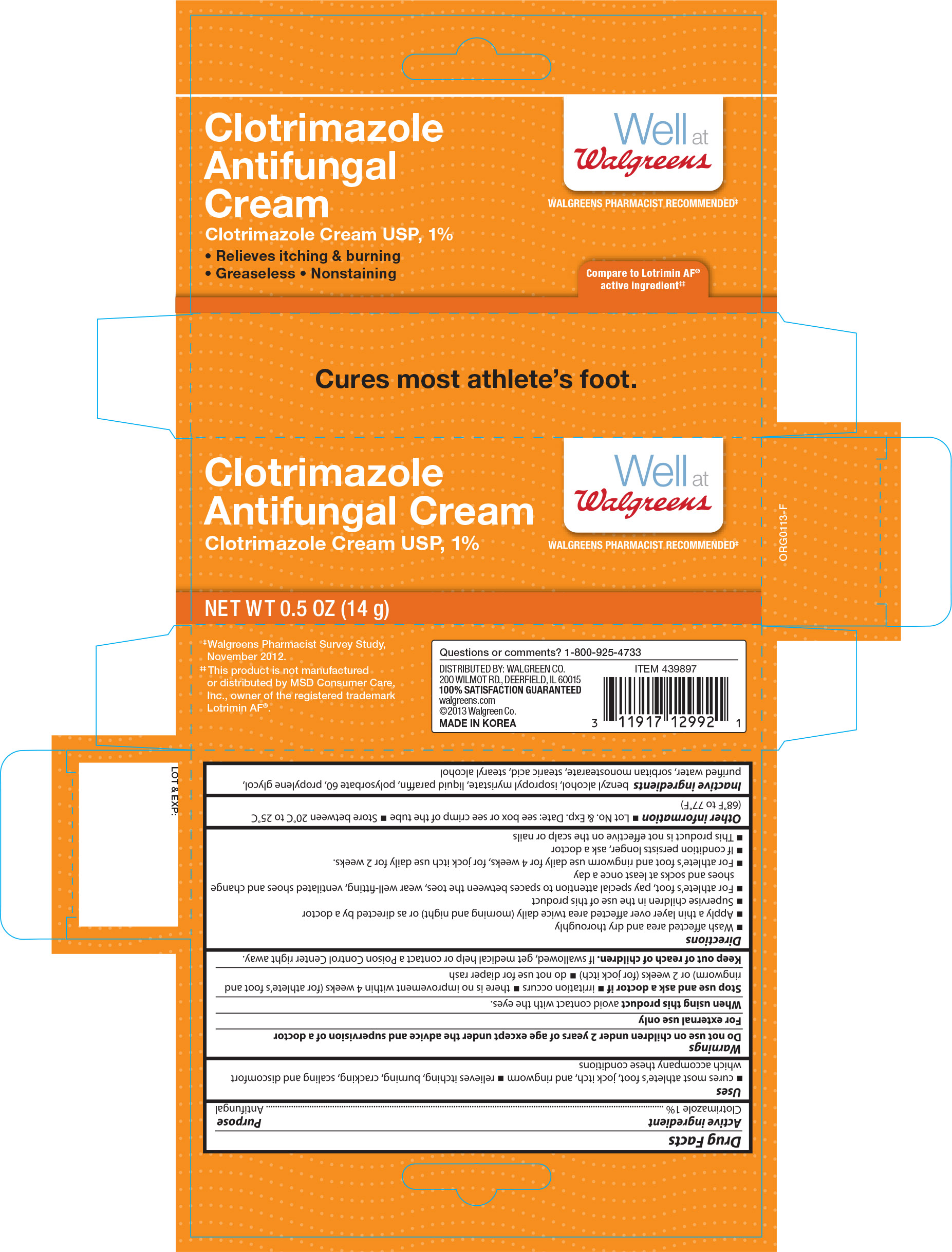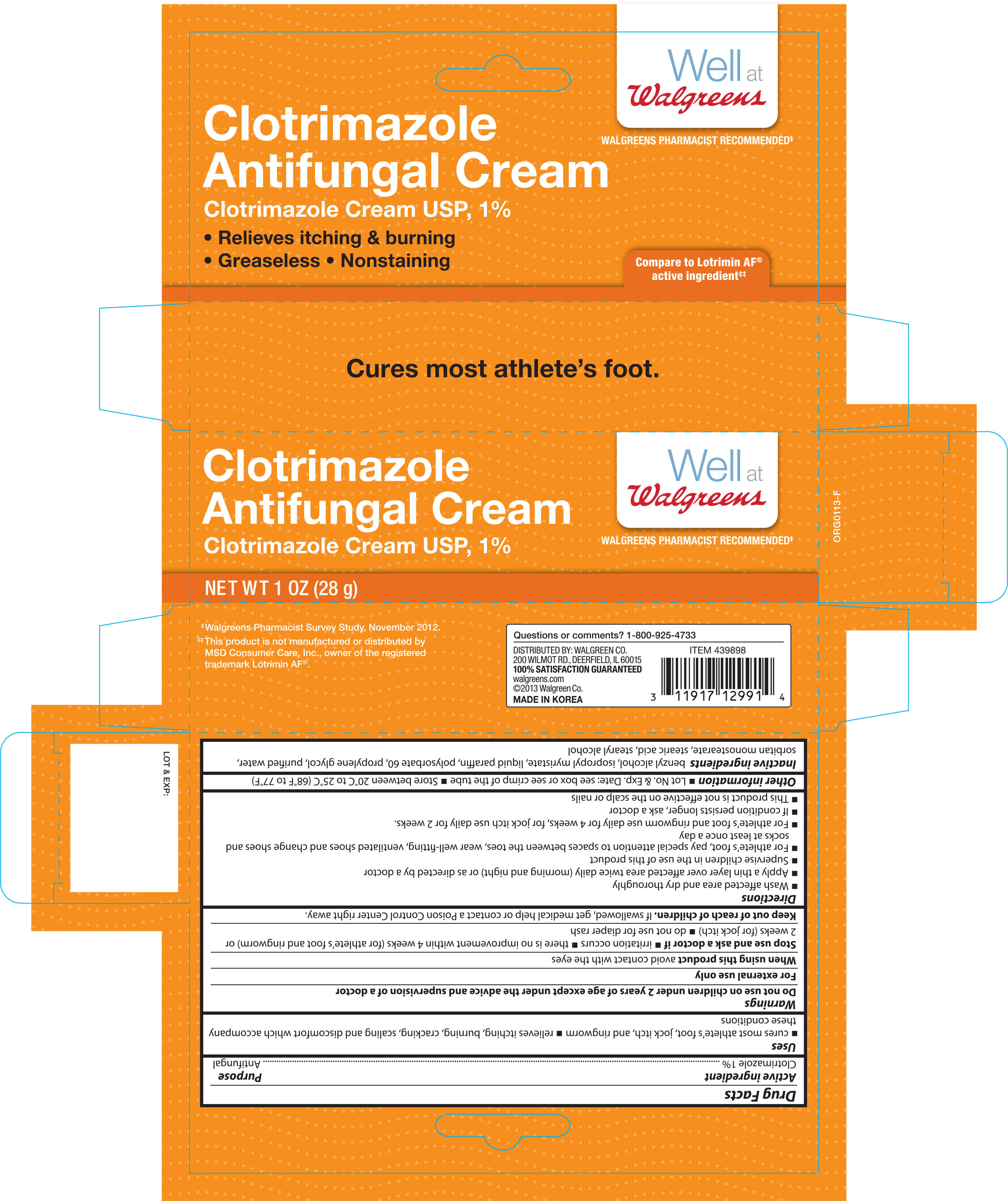 DRUG LABEL: WALGREENS CLOTRIMAZOLE
NDC: 0363-1299 | Form: CREAM
Manufacturer: WALGREEN CO
Category: otc | Type: HUMAN OTC DRUG LABEL
Date: 20161012

ACTIVE INGREDIENTS: CLOTRIMAZOLE 1 g/100 g
INACTIVE INGREDIENTS: BENZYL ALCOHOL; ISOPROPYL MYRISTATE; PARAFFIN; POLYSORBATE 60; PROPYLENE GLYCOL; WATER; SORBITAN MONOSTEARATE; STEARIC ACID; STEARYL ALCOHOL

Active ingredient Purpose

Clotrimazole 1% ........................................................................Antifungal

Uses

- cures most athlete's foot, jock itch, and ringworm
- relieves itching, burning, cracking, scaling and discomfort which accompany these conditions

Warnings

Do not use on children under 2 years of age except under the advice and supervision of a doctor

For external use only

When using this product avoid contact with the eyes

Stop use and ask a doctor if

- irritation occurs
- there is no improvement within 4 weeks (for athlete's foot and ringworm) or 2 weeks (jock itch)
- do not use for diaper rash

Keep out of reach of children.

If swallowed, get medical help or contact a Poison Control Center right away.

Directions

- wash affected area and dry thoroughly
- apply a thin layer over affected area twice daily (morning and night) or as directed by a doctor
- supervise children in the use of this product
- for athlete's foot, pay special attention to spaces between the toes, wear well-fitting, ventilated shoes and change shoes and sock at least once a day
- for athlete's foot and ringworm use daily for 4 weeks, for jock itch use daily for 2 weeks
- if conditions persist longer, ask a doctor
- this product is not effective on the scalp or nails

Other information

- Lot No. & Exp. Date: see box or see crimp of the tube
- Store between 20°C to 25°C (68°F to 77°F)

Inactive ingredients

benzyl alcohol, isopropyl myristate, liquid paraffin, polysorbate 60, propylene glycol, purified water, sorbitan monostearate, stearic acid, stearyl alcohol

DOSAGE AND ADMINISTRATION

Distributed by:

Walgreen Co.,

200 Wilmot Rd.

Deerfield, IL 60015-4616

Made in Korea